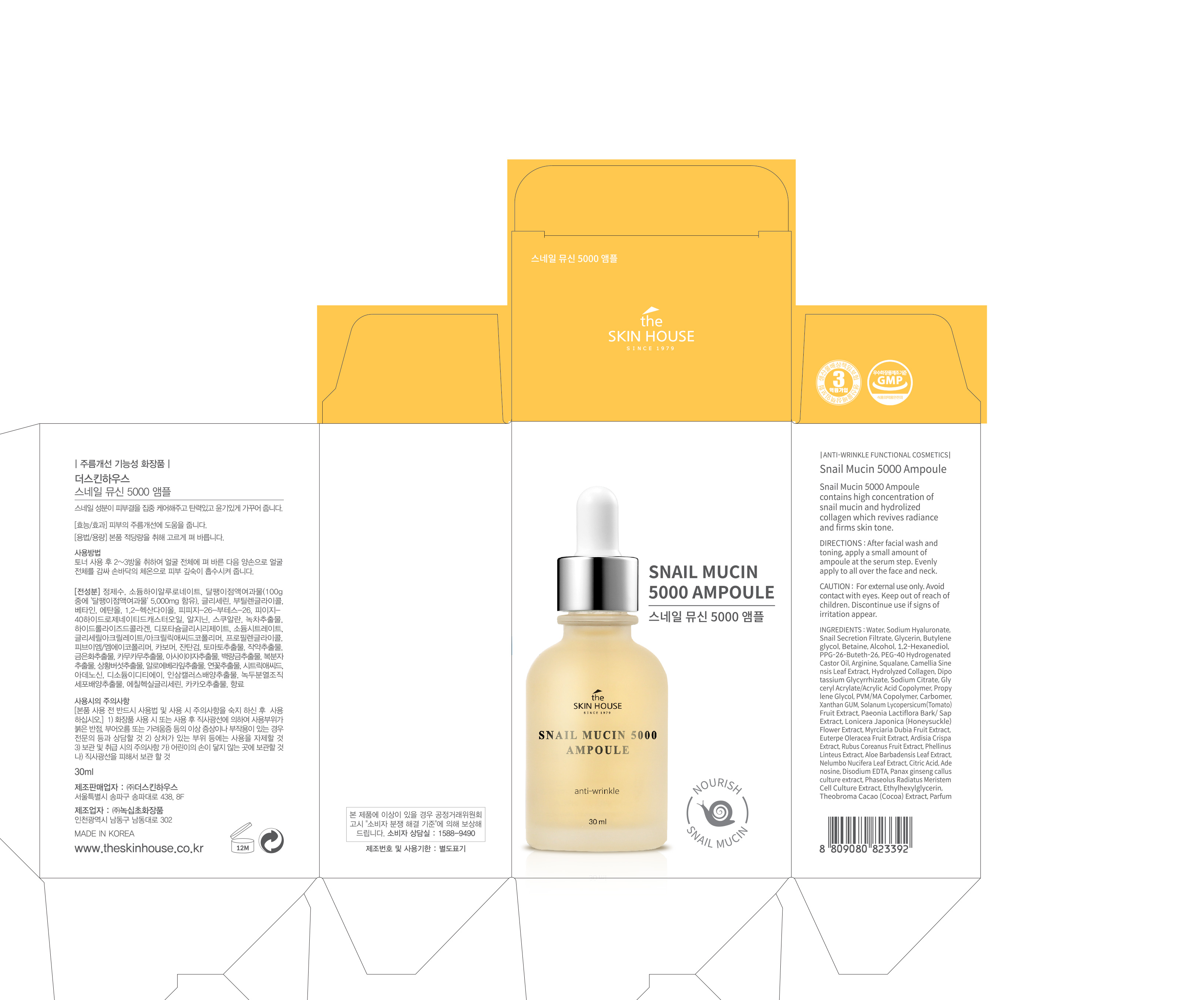 DRUG LABEL: THE SKIN HOUSE SNAIL MUCIN 5000 AMPOULE
NDC: 73590-0021 | Form: LIQUID
Manufacturer: NOKSIBCHO cosmetic Co., Ltd.
Category: otc | Type: HUMAN OTC DRUG LABEL
Date: 20200316

ACTIVE INGREDIENTS: SNAIL, UNSPECIFIED 0.1 g/100 mL
INACTIVE INGREDIENTS: WATER; BUTYLENE GLYCOL

Drug Facts

ACTIVE INGREDIENT

Snail Secretion Filtrate

INACTIVE INGREDIENT

Water
Sodium Hyaluronate
Phenoxy ethanol
Glycerin
Butylene glycol
Betaine
Alcohol
1,2-Hexanediol
PPG-26-Buteth-26
PEG-40 Hydrogenated Castor Oil
Arginine
Snail Secretion Filtrat
Propylene Glycol
Squalane
Camellia Sinensis Leaf Extract
Hydrolyzed Collagen
Dipotassium Glycyrrhizate
Sodium Citrate
Glyceryl Acrylate/Acrylic Acid Copolymer
PVM/MA Copolymer
Carbomer
Xanthan GUM
Solanum Lycopersicum (Tomato) Fruit Extract
Paeonia Lactiflora Bark/Sap Extract
Lonicera Japonica (Honeysuckle) Flower Extract
Myrciaria Dubia Fruit Extract
Euterpe Oleracea Fruit Extract
Ardisia Crispa Extract
Rubus Coreanus Fruit Extract
Phellinus Linteus Extract
Aloe Barbadensis Leaf Extract
Nelumbo Nucifera Leaf Extract
Citric Acid
Adenosine
Disodium EDTA
Panax ginseng culture extract
Caprylyl Glycol
Phaseolus Radiatus Seed Extract
Ethylhexylglycerin
Theobroma Cacao (Cocoa) Extract
Parfum

PURPOSE

anti-wrinkle function

keep out of reach of the children

INDICATIONS AND USAGE

apply proper amount and gently massage

WARNINGS

For external use only
When using this product

■ if the following symptoms occurs after use, stop use and consult with a skin specialist

red specks, swelling, itching

■ don’t use on the part where there is injury, eczema, or dermatitis

Keep out of reach of children

■ if swallowed, get medical help or contact a person control center immediately

DOSAGE AND ADMINISTRATION

for external use only